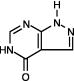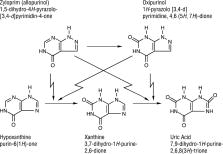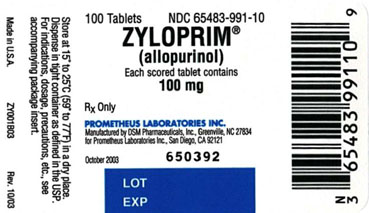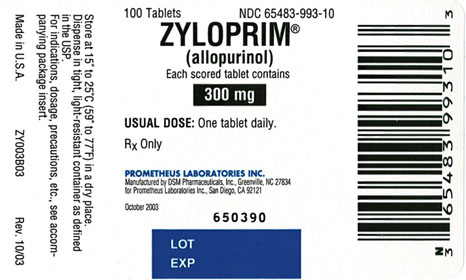 DRUG LABEL: ZYLOPRIM
NDC: 65483-991 | Form: TABLET
Manufacturer: Prometheus Laboratories Inc.
Category: prescription | Type: HUMAN PRESCRIPTION DRUG LABEL
Date: 20091130

ACTIVE INGREDIENTS: allopurinol 100 mg/1 1
INACTIVE INGREDIENTS: lactose; magnesium stearate; starch, potato; povidone

PRODUCT INFORMATION
ZYLOPRIM® (allopurinol)
100-mg Scored Tablets and
300-mg Scored Tablets

Rx Only

DESCRIPTION

ZYLOPRIM (allopurinol) has the following structural formula:

ZYLOPRIM is known chemically as 1,5-dihydro-4H-pyrazolo [3,4-d]pyrimidin-4-one. It is a xanthine oxidase inhibitor which is administered orally. Each scored white tablet contains 100 mg allopurinol and the inactive ingredients lactose, magnesium stearate, potato starch, and povidone. Each scored peach tablet contains 300 mg allopurinol and the inactive ingredients corn starch, FD&C Yellow No. 6 Lake, lactose, magnesium stearate, and povidone. Its solubility in water at 37°C is 80.0 mg/dL and is greater in an alkaline solution.

CLINICAL PHARMACOLOGY

ZYLOPRIM acts on purine catabolism, without disrupting the biosynthesis of purines. It reduces the production of uric acid by inhibiting the biochemical reactions immediately preceding its formation.

ZYLOPRIM is a structural analogue of the natural purine base, hypoxanthine. It is an inhiboitor of xanthine oxidase, the enzyme responsible for the conversion of hypoxanthine to xanthine and of xanthine to uric acid, the end product of purine metabolism in man. ZYLOPRIM is metabolized to the corresponding xanthine analogue, oxipurinol (alloxanthine), which also is an inhibitor of xanthine oxidase.

It has been shown that reutilization of both hypoxanthine and xanthine for nucleotide and nucleic acid synthesis is markedly enhanced when their oxidations are inhibited by ZYLOPRIM and oxipurinol. This reutilization does not disrupt normal nucleic acid anabolism, however, because feedback inhibition is an integral part of purine biosynthesis. As a result of xanthine oxidase inhibition, the serum concentration of hypoxanthine plus xanthine in patients receiving ZYLOPRIM for treatment of hyperuricemia is usually in the range of 0.3 to 0.4 mg/dL compared to a normal level of approximately 0.15 mg/dL. A maximum of 0.9 mg/dL of these oxypurines has been reported when the serum urate was lowered to less than 2 mg/dL by high doses of ZYLOPRIM. These values are far below the saturation levels at which point their precipitation would be expected to occur (above 7 mg/dL).

The renal clearance of hypoxanthine and xanthine is at least 10 times greater than that of uric acid. The increased xanthine and hypoxanthine in the urine have not been accompanied by problems of nephrolithiasis. Xanthine crystalluria has been reported in only three patients. Two of the patients had Lesch-Nyhan syndrome, which is characterized by excessive uric acid production combined with a deficiency of the enzyme, hypoxanthineguanine phosphoribosyltransferase (HGPRTase). This enzyme is required for the conversion of hypoxanthine, xanthine, and guanine to their respective nucleotides. The third patient had lymphosarcoma and produced an extremely large amount of uric acid because of rapid cell lysis during chemotherapy.

ZYLOPRIM is approximately 90% absorbed from the gastrointestinal tract. Peak plasma levels generally occur at 1.5 hours and 4.5 hours for ZYLOPRIM and oxipurinol respectively, and after a single oral dose of 300 mg ZYLOPRIM, maximum plasma levels of about 3 mcg/mL of ZYLOPRIM and 6.5 mcg/mL of oxipurinol are produced.

Approximately 20% of the ingested ZYLOPRIM is excreted in the feces. Because of its rapid oxidation to oxipurinol and a renal clearance rate approximately that of glomerular filtration rate, ZYLOPRIM has a plasma half-life of about 1 to 2 hours. Oxipurinol, however, has a longer plasma half-life (approximately 15 hours) and therefore effective xanthine oxidase inhibition is maintained over a 24-hour period with single daily doses of ZYLOPRIM. Whereas ZYLOPRIM is cleared essentially by glomerular filtration, oxipurinol is reabsorbed in the kidney tubules in a manner similar to the reabsorption of uric acid.

The clearance of oxipurinol is increased by uricosuric drugs, and as a consequence, the addition of a uricosuric agent reduces to some degree the inhibition of xanthine oxidase by oxipurinol and increases to some degree the urinary excretion of uric acid. In practice, the net effect of such combined therapy may be useful in some patients in achieving minimum serum uric acid levels provided the total urinary uric acid load does not exceed the competence of the patient's renal function.

Hyperuricemia may be primary, as in gout, or secondary to diseases such as acute and chronic leukemia, polycythemia vera, multiple myeloma, and psoriasis. It may occur with the use of diuretic agents, during renal dialysis, in the presence of renal damage, during starvation or reducing diets, and in the treatment of neoplastic disease where rapid resolution of tissue masses may occur. Asymptomatic hyperuricemia is not an indication for treatment with ZYLOPRIM (see INDICATIONS AND USAGE).

Gout is a metabolic disorder which is characterized by hyperuricemia and resultant deposition of monosodium urate in the tissues, particularly the joints and kidneys. The etiology of this hyperuricemia is the overproduction of uric acid in relation to the patient's ability to excrete it. If progressive deposition of urates is to be arrested or reversed, it is necessary to reduce the serum uric acid level below the saturation point to suppress urate precipitation.

Administration of ZYLOPRIM generally results in a fall in both serum and urinary uric acid within 2 to 3 days. The degree of this decrease can be manipulated almost at will since it is dose-dependent. A week or more of treatment with ZYLOPRIM may be required before its full effects are manifested; likewise, uric acid may return to pretreatment levels slowly (usually after a period of 7 to 10 days following cessation of therapy). This reflects primarily the accumulation and slow clearance of oxipurinol. In some patients a dramatic fall in urinary uric acid excretion may not occur, particularly in those with severe tophaceous gout. It has been postulated that this may be due to the mobilization of urate from tissue deposits as the serum uric acid level begins to fall.

The action of ZYLOPRIM differs from that of uricosuric agents, which lower the serum uric acid level by increasing urinary excretion of uric acid. ZYLOPRIM reduces both the serum and urinary uric acid levels by inhibiting the formation of uric acid. The use of ZYLOPRIM to block the formation of urates avoids the hazard of increased renal excretion of uric acid posed by uricosuric drugs.

ZYLOPRIM can substantially reduce serum and urinary uric acid levels in previously refractory patients even in the presence of renal damage serious enough to render uricosuric drugs virtually ineffective. Salicylates may be given conjointly for their antirheumatic effect without compromising the action of ZYLOPRIM. This is in contrast to the nullifying effect of salicylates on uricosuric drugs.

ZYLOPRIM also inhibits the enzymatic oxidation of mercaptopurine, the sulfur-containing analogue of hypoxanthine, to 6-thiouric acid. This oxidation, which is catalyzed by xanthine oxidase, inactivates mercaptopurine. Hence, the inhibition of such oxidation by ZYLOPRIM may result in as much as a 75% reduction in the therapeutic dose requirement of mercaptopurine when the two compounds are given together.

INDICATIONS AND USAGE

THIS IS NOT AN INNOCUOUS DRUG. IT IS NOT RECOMMENDED FOR THE TREATMENT OF ASYMPTOMATIC HYPERURICEMIA.

ZYLOPRIM reduces serum and urinary uric acid concentrations. Its use should be individualized for each patient and requires an understanding of its mode of action and pharmacokinetics (see CLINICAL PHARMACOLOGY, CONTRAINDICATIONS, WARNINGS, and PRECAUTIONS).

ZYLOPRIM is indicated in:

1. the management of patients with signs and symptoms of primary or secondary gout (acute attacks, tophi, joint destruction, uric acid lithiasis, and/or nephropathy).
2. the management of patients with leukemia, lymphoma and malignancies who are receiving cancer therapy which causes elevations of serum and urinary uric acid levels. Treatment with ZYLOPRIM should be discontinued when the potential for overproduction of uric acid is no longer present.
3. the management of patients with recurrent calcium oxalate calculi whose daily uric acid excretion exceeds 800 mg/day in male patients and 750 mg/day in female patients. Therapy in such patients should be carefully assessed initially and reassessed periodically to determine in each case that treatment is beneficial and that the benefits outweigh the risks.

CONTRAINDICATIONS

Patients who have developed a severe reaction to ZYLOPRIM should not be restarted on the drug.

WARNINGS

ZYLOPRIM SHOULD BE DISCONTINUED AT THE FIRST APPEARANCE OF SKIN RASH OR OTHER SIGNS WHICH MAY INDICATE AN ALLERGIC REACTION. In some instances a skin rash may be followed by more severe hypersensitivity reactions such as exfoliative, urticarial, and purpuric lesions, as well as Stevens-Johnson syndrome (erythema multiforme exudativum), and/or generalized vasculitis, irreversible hepatotoxicity, and, on rare occasions, death.

In patients receiving PURINETHOL® (mercaptopurine) or IMURAN® (azathioprine), the concomitant administration of 300 to 600 mg of ZYLOPRIM per day will require a reduction in dose to approximately one-third to one-fourth of the usual dose of mercaptopurine or azathioprine. Subsequent adjustment of doses of mercaptopurine or azathioprine should be made on the basis of therapeutic response and the appearance of toxic effects (see CLINICAL PHARMACOLOGY).

A few cases of reversible clinical hepatotoxicity have been noted in patients taking ZYLOPRIM, and in some patients, asymptomatic rises in serum alkaline phosphatase or serum transaminase have been observed. If anorexia, weight loss, or pruritus develop in patients on ZYLOPRIM, evaluation of liver function should be part of their diagnostic workup. In patients with pre-existing liver disease, periodic liver function tests are recommended during the early stages of therapy.

Due to the occasional occurrence of drowsiness, patients should be alerted to the need for due precaution when engaging in activities where alertness is mandatory.

The occurrence of hypersensitivity reactions to ZYLOPRIM may be increased in patients with decreased renal function receiving thiazides and ZYLOPRIM concurrently. For this reason, in this clinical setting, such combinations should be administered with caution and patients should be observed closely.

PRECAUTIONS

GENERAL PRECAUTIONS

General: An increase in acute attacks of gout has been reported during the early stages of administration of ZYLOPRIM , even when normal or subnormal serum uric acid levels have been attained. Accordingly, maintenance doses of colchicine generally should be given prophylactically when ZYLOPRIM is begun. In addition, it is recommended that the patient start with a low dose of ZYLOPRIM (100 mg daily) and increase at weekly intervals by 100 mg until a serum uric acid level of 6 mg/dL or less is attained but without exceeding the maximum recommended dose (800 mg per day). The use of colchicine or anti-inflammatory agents may be required to suppress gouty attacks in some cases. The attacks usually become shorter and less severe after several months of therapy. The mobilization of urates from tissue deposits which cause fluctuations in the serum uric acid levels may be a possible explanation for these episodes. Even with adequate therapy with ZYLOPRIM, it may require several months to deplete the uric acid pool sufficiently to achieve control of the acute attacks.

A fluid intake sufficient to yield a daily urinary output of at least 2 liters and the maintenance of a neutral or, preferably, slightly alkaline urine are desirable to (1) avoid the theoretical possibility of formation of xanthine calculi under the influence of therapy with ZYLOPRIM and (2) help prevent renal precipitation of urates in patients receiving concomitant uricosuric agents.

Some patients with pre-existing renal disease or poor urate clearance have shown a rise in BUN during administration of ZYLOPRIM. Although the mechanism responsible for this has not been established, patients with impaired renal function should be carefully observed during the early stages of administration of ZYLOPRIM and the dosage decreased or the drug withdrawn if increased abnormalities in renal function appear and persist.

Renal failure in association with administration of ZYLOPRIM has been observed among patients with hyperuricemia secondary to neoplastic diseases. Concurrent conditions such as multiple myeloma and congestive myocardial disease were present among those patients whose renal dysfunction increased after ZYLOPRIM was begun. Renal failure is also frequently associated with gouty nephropathy and rarely with hypersensitivity reactions associated with ZYLOPRIM. Albuminuria has been observed among patients who developed clinical gout following chronic glomerulonephritis and chronic pyelonephritis.

Patients with decreased renal function require lower doses of ZYLOPRIM than those with normal renal function. Lower than recommended doses should be used to initiate therapy in any patients with decreased renal function and they should be observed closely during the early stages of administration of ZYLOPRIM . In patients with severely impaired renal function or decreased urate clearance, the half-life of oxipurinol in the plasma is greatly prolonged. Therefore, a dose of 100 mg per day or 300 mg twice a week, or perhaps less, may be sufficient to maintain adequate xanthine oxidase inhibition to reduce serum urate levels.

Bone marrow depression has been reported in patients receiving ZYLOPRIM, most of whom received concomitant drugs with the potential for causing this reaction. This has occurred as early as 6 weeks to as long as 6 years after the initiation of therapy of ZYLOPRIM . Rarely, a patient may develop varying degrees of bone marrow depression, affecting one or more cell lines, while receiving ZYLOPRIM alone.

PATIENT COUNSELING INFORMATION

Information for Patients: Patients should be informed of the following:

(1) They should be cautioned to discontinue ZYLOPRIM and to consult their physician immediately at the first sign of a skin rash, painful urination, blood in the urine, irritation of the eyes, or swelling of the lips or mouth. (2) They should be reminded to continue drug therapy prescribed for gouty attacks since optimal benefit of ZYLOPRIM may be delayed for 2 to 6 weeks. (3) They should be encouraged to increase fluid intake during therapy to prevent renal stones. (4) If a single dose of ZYLOPRIM is occasionally forgotten, there is no need to double the dose at the next scheduled time. (5) There may be certain risks associated with the concomitant use of ZYLOPRIM and dicumarol, sulfinpyrazone, mercaptopurine, azathioprine, ampicillin, amoxicillin, and thiazide diuretics, and they should follow the instructions of their physician. (6) Due to the occasional occurrence of drowsiness, patients should take precautions when engaging in activities where alertness is mandatory. (7) Patients may wish to take ZYLOPRIM after meals to minimize gastric irritation.

LABORATORY TESTS

Laboratory Tests: The correct dosage and schedule for maintaining the serum uric acid within the normal range is best determined by using the serum uric acid as an index.

In patients with pre-existing liver disease, periodic liver function tests are recommended during the early stages of therapy (see WARNINGS).

ZYLOPRIM and its primary active metabolite, oxipurinol, are eliminated by the kidneys; therefore, changes in renal function have a profound effect on dosage. In patients with decreased renal function or who have concurrent illnesses which can affect renal function such as hypertension and diabetes mellitus, periodic laboratory parameters of renal function, particularly BUN and serum creatinine or creatinine clearance, should be performed and the patient's dosage of ZYLOPRIM reassessed.

The prothrombin time should be reassessed periodically in the patients receiving dicumarol who are given ZYLOPRIM.

DRUG INTERACTIONS

Drug Interactions: In patients receiving PURINETHOL (mercaptopurine) or IMURAN (azathioprine), the concomitant administration of 300 to 600 mg of ZYLOPRIM per day will require a reduction in dose to approximately one third to one fourth of the usual dose of mercaptopurine or azathioprine. Subsequent adjustment of doses of mercaptopurine or azathioprine should be made on the basis of therapeutic response and the appearance of toxic effects (see CLINICAL PHARMACOLOGY).

It has been reported that ZYLOPRIM prolongs the half-life of the anticoagulant, dicumarol. The clinical basis of this drug interaction has not been established but should be noted when ZYLOPRIM is given to patients already on dicumarol therapy.

Since the excretion of oxipurinol is similar to that of urate, uricosuric agents, which increase the excretion of urate, are also likely to increase the excretion of oxipurinol and thus lower the degree of inhibition of xanthine oxidase. The concomitant administration of uricosuric agents and ZYLOPRIM has been associated with a decrease in the excretion of oxypurines (hypoxanthine and xanthine) and an increase in urinary uric acid excretion compared with that observed with ZYLOPRIM alone. Although clinical evidence to date has not demonstrated renal precipitation of oxypurines in patients either on ZYLOPRIM alone or in combination with uricosuric agents, the possibility should be kept in mind.

The reports that the concomitant use of ZYLOPRIM and thiazide diuretics may contribute to the enhancement of allopurinol toxicity in some patients have been reviewed in an attempt to establish a cause-and-effect relationship and a mechanism of causation. Review of these case reports indicates that the patients were mainly receiving thiazide diuretics for hypertension and that tests to rule out decreased renal function secondary to hypertensive nephropathy were not often performed. In those patients in whom renal insufficiency was documented, however, the recommendation to lower the dose of ZYLOPRIM was not followed. Although a causal mechanism and a cause-and-effect relationship have not been established, current evidence suggests that renal function should be monitored in patients on thiazide diuretics and ZYLOPRIM even in the absence of renal failure, and dosage levels should be even more conservatively adjusted in those patients on such combined therapy if diminished renal function is detected.

An increase in the frequency of skin rash has been reported among patients receiving ampicillin or amoxicillin concurrently with ZYLOPRIM compared to patients who are not receiving both drugs. The cause of the reported association has not been established.

Enhanced bone marrow suppression by cyclophosphamide and other cytotoxic agents has been reported among patients with neoplastic disease, except leukemia, in the presence of ZYLOPRIM. However, in a well-controlled study of patients with lymphoma on combination therapy, ZYLOPRIM did not increase the marrow toxicity of patients treated with cyclophosphamide, doxorubicin, bleomycin, procarbazine, and/or mechlorethamine.

Tolbutamide's conversion to inactive metabolites has been shown to be catalyzed by xanthine oxidase from rat liver. The clinical significance, if any, of these observations is unknown.

Chlorpropamide's plasma half-life may be prolonged by ZYLOPRIM, since ZYLOPRIM and chlorpropamide may compete for excretion in the renal tubule. The risk of hypoglycemia secondary to this mechanism may be increased if ZYLOPRIM and chlorpropamide are given concomitantly in the presence of renal insufficiency.

Rare reports indicate that cyclosporine levels may be increased during concomitant treatment with ZYLOPRIM. Monitoring of cyclosporine levels and possible adjustment of cyclosporine dosage should be considered when these drugs are co-administered.

DRUG AND OR LABORATORY TEST INTERACTIONS

Drug/Laboratory Test Interactions: ZYLOPRIM is not known to alter the accuracy of laboratory tests.

Pregnancy

TERATOGENIC EFFECTS

Teratogenic Effects: Pregnancy Category C. Reproductive studies have been performed in rats and rabbits at doses up to twenty times the usual human dose (5 mg/kg per day), and it was concluded that there was no impaired fertility or harm to the fetus due to allopurinol. There is a published report of a study in pregnant mice given 50 or 100 mg/kg allopurinol intraperitoneally on gestation days 10 or 13. There were increased numbers of dead fetuses in dams given 100 mg/kg allopurinol but not in those given 50 mg/kg. There were increased numbers of external malformations in fetuses at both doses of allopurinol on gestation day 10 and increased numbers of skeletal malformations in fetuses at both doses on gestation day 13. It cannot be determined whether this represented a fetal effect or an effect secondary to maternal toxicity. There are, however, no adequate or well-controlled studies in pregnant women. Because animal reproduction studies are not always predictive of human response, this drug should be used during pregnancy only if clearly needed.

Experience with ZYLOPRIM during human pregnancy has been limited partly because women of reproductive age rarely require treatment with ZYLOPRIM. There are two unpublished reports and one published paper of women giving birth to normal offspring after receiving ZYLOPRIM during pregnancy.

NURSING MOTHERS

Nursing Mothers: Allopurinol and oxipurinol have been found in the milk of a mother who was receiving ZYLOPRIM. Since the effect of allopurinol on the nursing infant is unknown, caution should be exercised when ZYLOPRIM is administered to a nursing woman.

PEDIATRIC USE

Pediatric Use: ZYLOPRIM is rarely indicated for use in children with the exception of those with hyperuricemia secondary to malignancy or to certain rare inborn errors of purine metabolism (see INDICATIONS AND USAGE and DOSAGE AND ADMINISTRATION).

ADVERSE REACTIONS

Data upon which the following estimates of incidence of adverse reactions are made are derived from experiences reported in the literature, unpublished clinical trials and voluntary reports since marketing of ZYLOPRIM (allopurinol) began. Past experience suggested that the most frequent event following the initiation of allopurinol treatment was an increase in acute attacks of gout (average 6% in early studies). An analysis of current usage suggests that the incidence of acute gouty attacks has diminished to less than 1%. The explanation for this decrease has not been determined but may be due in part to initiating therapy more gradually (see PRECAUTIONS and DOSAGE AND ADMINISTRATION).

The most frequent adverse reaction to ZYLOPRIM is skin rash. Skin reactions can be severe and sometimes fatal. Therefore, treatment with ZYLOPRIM should be discontinued immediately if a rash develops (see WARNINGS). Some patients with the most severe reaction also had fever, chills, arthralgias, cholestatic jaundice, eosinophilia and mild leukocytosis or leukopenia. Among 55 patients with gout treated with ZYLOPRIM for 3 to 34 months (average greater than 1 year) and followed prospectively, Rundles observed that 3% of patients developed a type of drug reaction which was predominantly a pruritic maculopapular skin eruption, sometimes scaly or exfoliative. However, with current usage, skin reactions have been observed less frequently than 1%. The explanation for this decrease is not obvious. The incidence of skin rash may be increased in the presence of renal insufficiency. The frequency of skin rash among patients receiving ampicillin or amoxicillin concurrently with ZYLOPRIM has been reported to be increased (see PRECAUTIONS).

Most Common Reactions* Probably Causally Related:

Gastrointestinal: Diarrhea, nausea, alkaline phosphatase increase, SGOT/SGPT increase.
Metabolic and Nutritional: Acute attacks of gout.
Skin and Appendages: Rash, maculopapular rash.
*Early clinical studies and incidence rates from early clinical experience with ZYLOPRIM suggested that these adverse reactions were found to occur at a rate of greater than 1%. The most frequent event observed was acute attacks of gout following the initiation of therapy. Analyses of current usage suggest that the incidence of these adverse reactions is now less than 1%. The explanation for this decrease has not been determined, but it may be due to following recommended usage (see ADVERSE REACTIONS introduction, INDICATIONS AND USAGE, PRECAUTIONS, and DOSAGE AND ADMINISTRATION).

Incidence Less Than 1% Probably Causally Related:

Body As a Whole: Ecchymosis, fever, headache.
Cardiovascular: Necrotizing angiitis, vasculitis.
Gastrointestinal: Hepatic necrosis, granulomatous hepatitis, hepatomegaly, hyperbilirubinemia, cholestatic jaundice, vomiting, intermittent abdominal pain, gastritis, dyspepsia.
Hemic and Lymphatic: Thrombocytopenia, eosinophilia, leukocytosis, leukopenia.
Musculoskeletal: Myopathy, arthralgias.
Nervous: Peripheral neuropathy, neuritis, paresthesia, somnolence.
Respiratory: Epistaxis.
Skin and Appendages: Erythema multiforme exudativum (Stevens-Johnson syndrome), toxic epidermal necrolysis (Lyell's syndrome), hypersensitivity vasculitis, purpura, vesicular bullous dermatitis, exfoliative dermatitis, eczematoid dermatitis, pruritus, urticaria, alopecia, onycholysis, lichen planus.
Special Senses: Taste loss/perversion.
Urogenital: Renal failure, uremia (see PRECAUTIONS).

Incidence Less Than 1% Causal Relationship Unknown:

Body As a Whole: Malaise.
Cardiovascular: Pericarditis, peripheral vascular disease, thrombophlebitis, bradycardia, vasodilation.
Endocrine: Infertility (male), hypercalcemia, gynecomastia (male).
Gastrointestinal: Hemorrhagic pancreatitis, gastrointestinal bleeding, stomatitis, salivary gland swelling, hyperlipidemia, tongue edema, anorexia.
Hemic and Lymphatic: Aplastic anemia, agranulocytosis, eosinophilic fibrohistiocytic lesion of bone marrow, pancytopenia, prothrombin decrease, anemia, hemolytic anemia, reticulocytosis, lymphadenopathy, lymphocytosis.
Musculoskeletal: Myalgia.
Nervous: Optic neuritis, confusion, dizziness, vertigo, foot drop, decrease in libido, depression, amnesia, tinnitus, asthenia, insomnia.
Respiratory: Bronchospasm, asthma, pharyngitis, rhinitis.
Skin and Appendages: Furunculosis, facial edema, sweating, skin edema.
Special Senses: Cataracts, macular retinitis, iritis, conjunctivitis, amblyopia.
Urogenital: Nephritis, impotence, primary hematuria, albuminuria.

OVERDOSAGE

Massive overdosing or acute poisoning by ZYLOPRIM has not been reported.

In mice, the 50% lethal dose (LD50) is 160 mg/kg given intraperitoneally (IP) with deaths delayed up to 5 days and 700 mg/kg orally (PO) (approximately 140 times the usual human dose) with deaths delayed up to 3 days. In rats, the acute LD50 is 750 mg/kg IP and 6000 mg/kg PO (approximately 1200 times the human dose).

In the management of overdosage there is no specific antidote for ZYLOPRIM. There has been no clinical experience in the management of a patient who has taken massive amounts of ZYLOPRIM.

Both ZYLOPRIM and oxipurinol are dialyzable; however, the usefulness of hemodialysis or peritoneal dialysis in the management of an overdose of ZYLOPRIM is unknown.

DOSAGE AND ADMINISTRATION

The dosage of ZYLOPRIM to accomplish full control of gout and to lower serum uric acid to normal or near-normal levels varies with the severity of the disease. The average is 200 to 300 mg/day for patients with mild gout and 400 to 600 mg/day for those with moderately severe tophaceous gout. The appropriate dosage may be administered in divided doses or as a single equivalent dose with the 300-mg tablet. Dosage requirements in excess of 300 mg should be administered in divided doses. The minimal effective dosage is 100 to 200 mg daily and the maximal recommended dosage is 800 mg daily. To reduce the possibility of flare-up of acute gouty attacks, it is recommended that the patient start with a low dose of ZYLOPRIM (100 mg daily) and increase at weekly intervals by 100 mg until a serum uric acid level of 6 mg/dL or less is attained but without exceeding the maximal recommended dosage.

Normal serum urate levels are usually achieved in 1 to 3 weeks. The upper limit of normal is about 7 mg/dL for men and postmenopausal women and 6 mg/dL for premenopausal women. Too much reliance should not be placed on a single serum uric acid determination since, for technical reasons, estimation of uric acid may be difficult. By selecting the appropriate dosage and, in certain patients, using uricosuric agents concurrently, it is possible to reduce serum uric acid to normal or, if desired, to as low as 2 to 3 mg/dL and keep it there indefinitely.

While adjusting the dosage of ZYLOPRIM in patients who are being treated with colchicine and/or anti-inflammatory agents, it is wise to continue the latter therapy until serum uric acid has been normalized and there has been freedom from acute gouty attacks for several months.

In transferring a patient from a uricosuric agent to ZYLOPRIM, the dose of the uricosuric agent should be gradually reduced over a period of several weeks and the dose of ZYLOPRIM gradually increased to the required dose needed to maintain a normal serum uric acid level.

It should also be noted that ZYLOPRIM is generally better tolerated if taken following meals. A fluid intake sufficient to yield a daily urinary output of at least 2 liters and the maintenance of a neutral or, preferably, slightly alkaline urine are desirable.

Since ZYLOPRIM and its metabolites are primarily eliminated only by the kidney, accumulation of the drug can occur in renal failure, and the dose of ZYLOPRIM should consequently be reduced. With a creatinine clearance of 10 to 20 mL/min, a daily dosage of 200 mg of ZYLOPRIM is suitable. When the creatinine clearance is less than 10 mL/min, the daily dosage should not exceed 100 mg. With extreme renal impairment (creatinine clearance less than 3 mL/min) the interval between doses may also need to be lengthened.

The correct size and frequency of dosage for maintaining the serum uric acid just within the normal range is best determined by using the serum uric acid level as an index.

For the prevention of uric acid nephropathy during the vigorous therapy of neoplastic disease, treatment with 600 to 800 mg daily for 2 or 3 days is advisable together with a high fluid intake. Otherwise similar considerations to the above recommendations for treating patients with gout govern the regulation of dosage for maintenance purposes in secondary hyperuricemia.

The dose of ZYLOPRIM recommended for management of recurrent calcium oxalate stones in hyperuricosuric patients is 200 to 300 mg/day in divided doses or as the single equivalent. This dose may be adjusted up or down depending upon the resultant control of the hyperuricosuria based upon subsequent 24 hour urinary urate determinations. Clinical experience suggests that patients with recurrent calcium oxalate stones may also benefit from dietary changes such as the reduction of animal protein, sodium, refined sugars, oxalate-rich foods, and excessive calcium intake, as well as an increase in oral fluids and dietary fiber.

Children, 6 to 10 years of age, with secondary hyperuricemia associated with malignancies may be given 300 mg ZYLOPRIM daily while those under 6 years are generally given 150 mg daily. The response is evaluated after approximately 48 hours of therapy and a dosage adjustment is made if necessary.

HOW SUPPLIED

100-mg (white) scored, flat cylindrical tablets imprinted with “ZYLOPRIM 100” on a raised hexagon, bottles of 100 (NDC 65483-991-10).

Store at 15° to 25°C (59° to 77°F) in a dry place.

300-mg (peach) scored, flat, cylindrical tablets imprinted with “ZYLOPRIM 300” on a raised hexagon, bottles of 100 (NDC 65483-993-10) and 500 (NDC 65483-993-50).

Store at 15° to 25°C (59° to 77°F) in a dry place and protect from light.

PROMETHEUS LABORATORIES INC.
Manufactured by
DSM Pharmaceuticals, Inc.
Greenville, NC 27834
for Prometheus Laboratories Inc.
San Diego, CA 92121

October 2003
ZY004B03

100 mg 100 Tablets Bottle

100 Tablets NDC 65483-991-10

ZYLOPRIM®

(allopurinol)

Each scored tablet contains

100 mg

Rx Only

PROMETHEUS LABORATORIES INC.

Manufactured by DSM Pharmaceuticals, Inc., Greenville, NC 27834

For Prometheus Laboratories Inc., San Diego, CA 92121

October 2003 650392

300 mg 100 Tablets Bottle

100 Tablets NDC 65483-993-10

ZYLOPRIM®

(allopurinol)

Each scored tablet contains

300 mg

Rx Only

PROMETHEUS LABORATORIES INC.

Manufactured by DSM Pharmaceuticals, Inc., Greenville, NC 27834

For Prometheus Laboratories Inc., San Diego, CA 92121

October 2003 650390